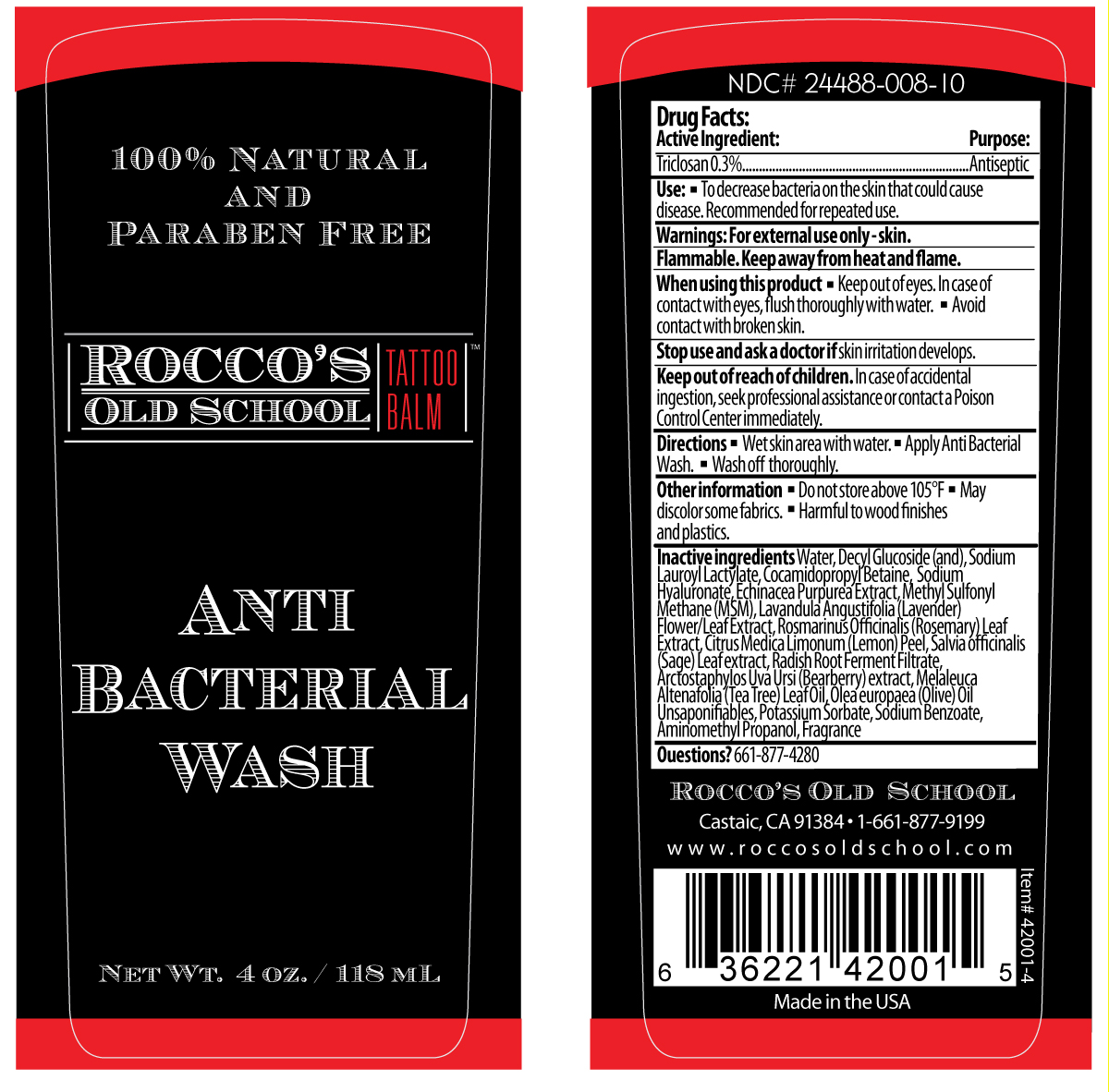 DRUG LABEL: Roccos Old School Tattoo Balm
NDC: 24488-008 | Form: LIQUID
Manufacturer: Rocco's Old School
Category: otc | Type: HUMAN OTC DRUG LABEL
Date: 20110228

ACTIVE INGREDIENTS: TRICLOSAN 3.54 mL/118 mL
INACTIVE INGREDIENTS: WATER; SODIUM LAUROYL LACTYLATE ; COCAMIDOPROPYL BETAINE; HYALURONATE SODIUM; ECHINACEA; DIMETHYL SULFONE; LAVANDULA ANGUSTIFOLIA FLOWERING TOP ; ROSEMARY; LEMON PEEL; SAGE; RADISH; ARCTOSTAPHYLOS UVA-URSI LEAF; TEA LEAF ; OLIVE OIL ; POTASSIUM SORBATE; SODIUM BENZOATE; AMINOMETHYLPROPANOL; COCONUT; LIME; VERBENA HASTATA ROOT 

Drug Facts

Active Ingredient:

Triclosan 0.3%...................................................Antiseptic

Use:

- To decrease bacteria on the skin that could cause disease. Recommended for repeated use.

Warnings:

For external use only--skin.

Flammable. Keep away from heat and flame.

When using this product

- Keep out of eyes. In case of contact with eyes, flush thoroughly with water.
- Avoid contact with broken skin.

Stop use and ask a doctor if

skin irritation develops.

Keep out of reach of children.

in case of accidental ingestion, seek professional assistance or contact a Poison Control Center immediately.

Directions

- Wet skin area with water.
- Apply Anti Bacterial Wash.
- Wash off thoroughly.

Other information

- Do not store above 105°F.
- May discolor some fabrics.
- Harmful to wood finishes and plastics.

Inactive ingredients

Water, Decyl Glucoside (and), Sodium Lauroyl Lactylate, Cocamidopropyl Betaine, Sodium Hyaluronate, Echinacea Purpurea Extract, Methyl Sulfonyl Methane (MSM), Lavandula Angustifolia (lavender) Flower/Leaf Extract, Rosmarinus Officinalis (Rosemary) Leaf Extract,Citrus Limonum (Lemon) Peel, Salvia Officinalis (Sage) Leaf Extract, Radish Root Ferment Filtrate, Arctostaphylos Uva Ursi (Bearberry) Extract, melaleuca Altenafolia (Tea Tree) Leaf Oil, Olea Europaea (Olive) Oil Unsaponifiables, Potassium Sorbate, SOdium Benzoate, Aminomethyl Propanol, Fragrance

Questions?

661-877-4280

PACKAGE LABEL

Placeholder text